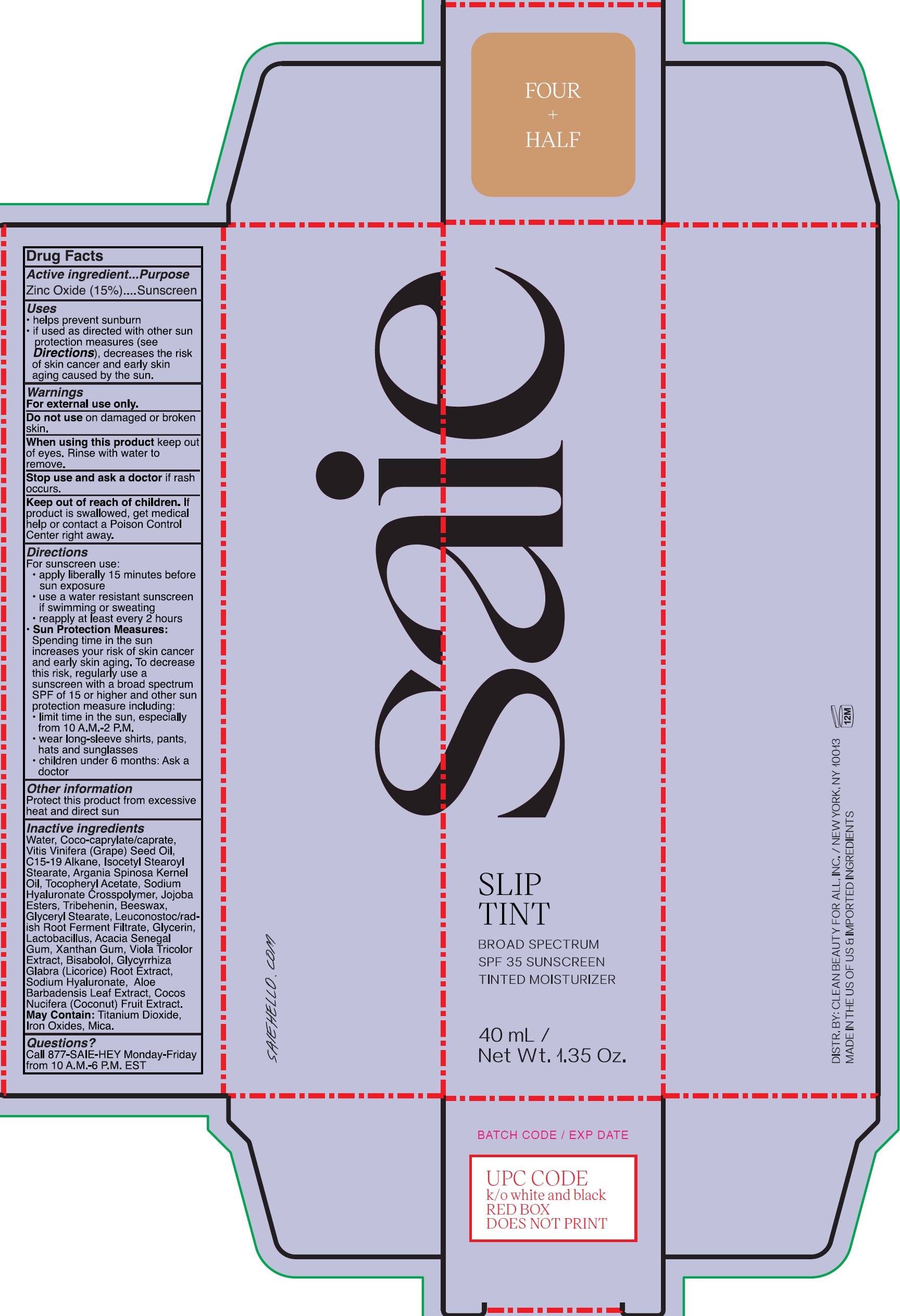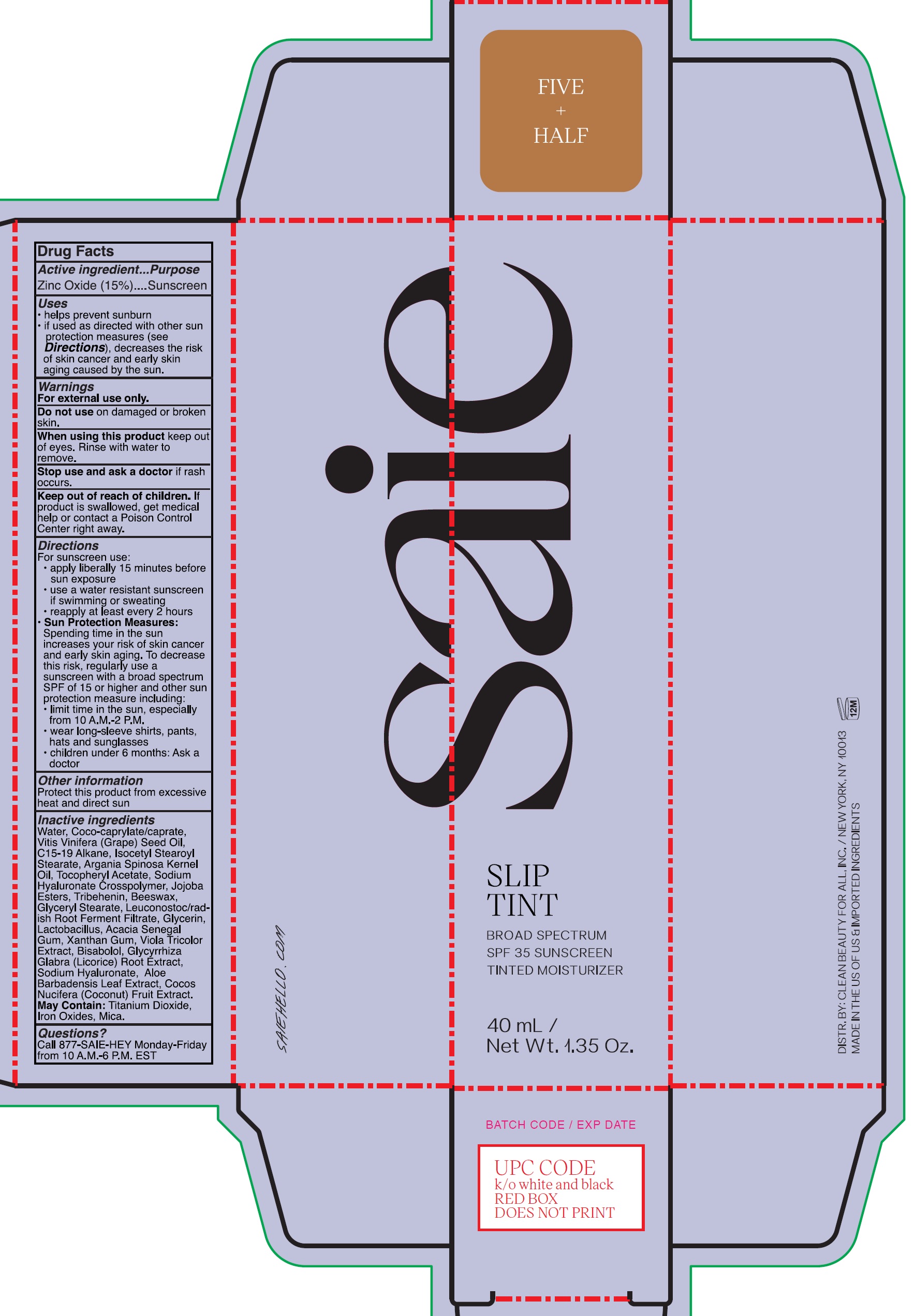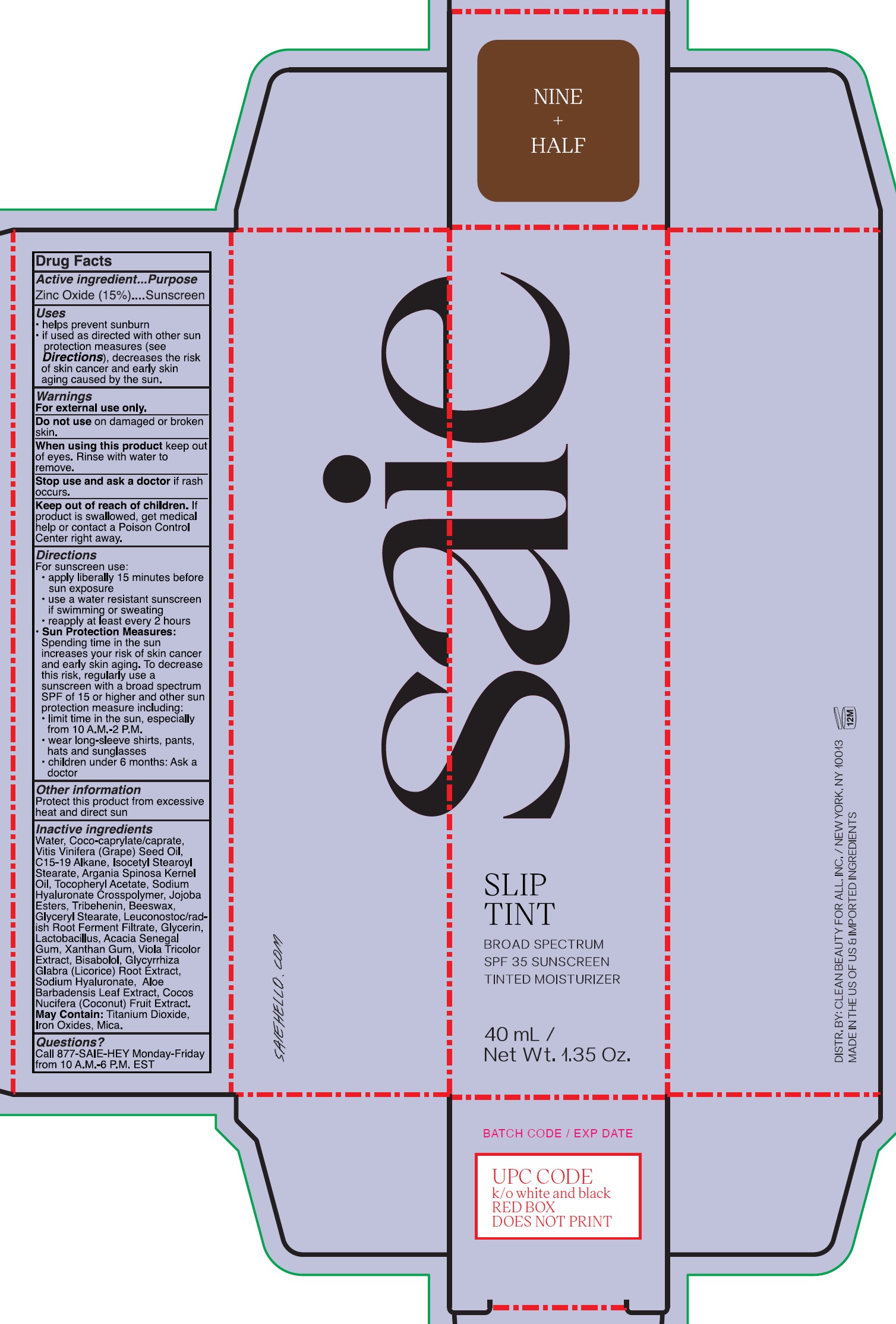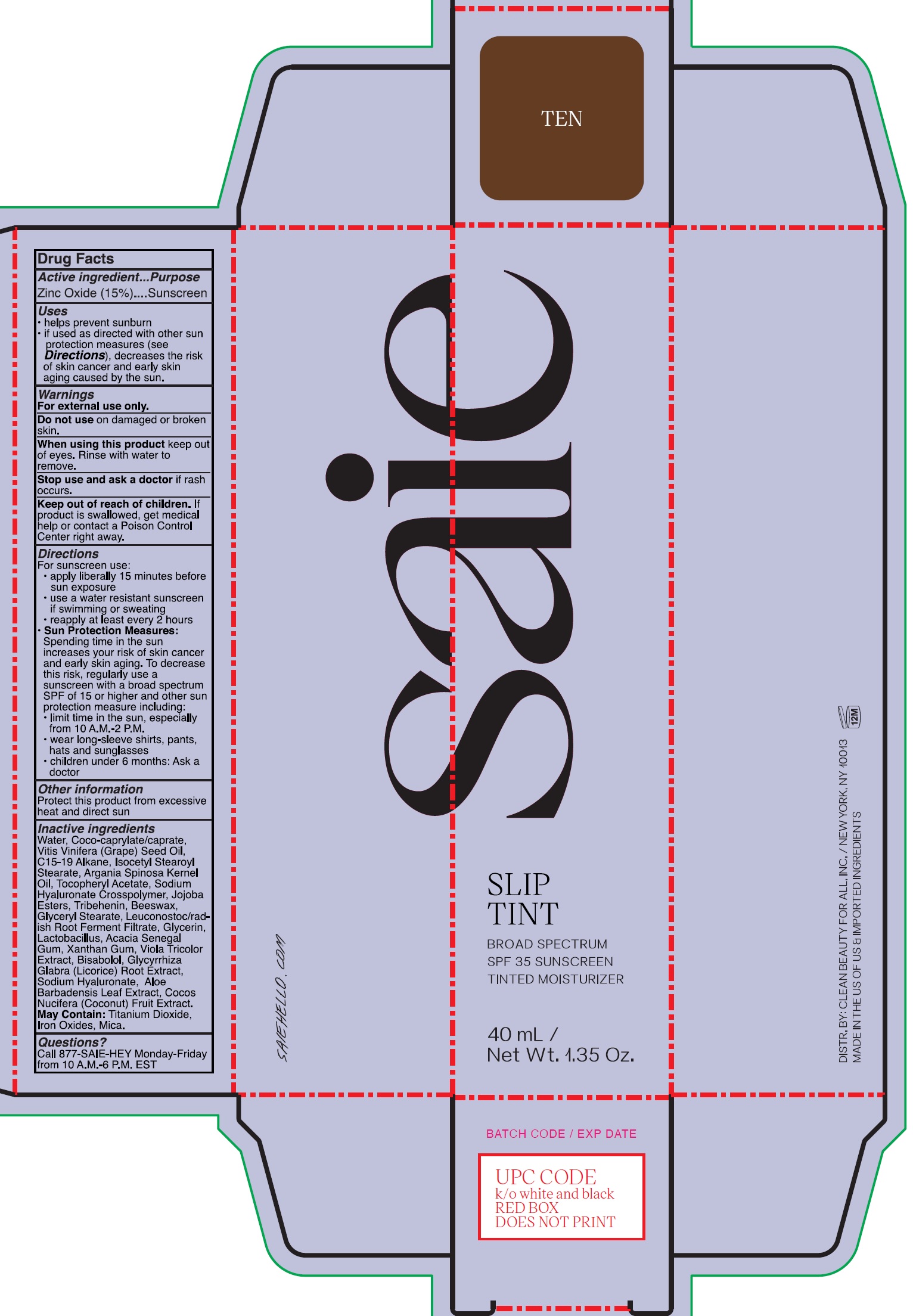 DRUG LABEL: Slip Tint Broad Spectrum SPF 35 Tinted Moisturizer
NDC: 90086-012 | Form: CREAM
Manufacturer: Clean Beauty For All, Inc
Category: otc | Type: HUMAN OTC DRUG LABEL
Date: 20231212

ACTIVE INGREDIENTS: ZINC OXIDE 150 mg/1 mL
INACTIVE INGREDIENTS: JOJOBA OIL, RANDOMIZED; WATER; COCO-CAPRYLATE/CAPRATE; GRAPE SEED OIL; C15-19 ALKANE; ISOCETYL STEAROYL STEARATE; ARGAN OIL; .ALPHA.-TOCOPHEROL ACETATE; TRIBEHENIN; YELLOW WAX; GLYCERYL MONOSTEARATE; LEUCONOSTOC/RADISH ROOT FERMENT FILTRATE; GLYCERIN; ACACIA; XANTHAN GUM; VIOLA TRICOLOR WHOLE; LEVOMENOL; GLYCYRRHIZA GLABRA; HYALURONATE SODIUM; ALOE VERA LEAF; COCONUT; LACTOBACILLUS ACIDOPHILUS

Slip Tint Broad Spectrum SPF 35 Tinted Moisturizer

Active ingredient

Zinc Oxide (15%)

Purpose

Sunscreen

Uses

- helps prevent sunburn
- if used as directed with other sun protection measures (see), decreases the risk of skin cancer and early skin aging caused by the sun. Directions

Warnings

For external use only.

Do not use

on damaged or broken skin.

When using this product

keep out of eyes. Rinse with water to remove.

Stop use and ask a doctor

if rash occurs.

Keep out of reach of children.

If product is swallowed, get medical help or contact a Poison Control Center right away.

Directions

For sunscreen use:

Spending time in the sun increases your risk of skin cancer and early skin aging. To decrease this risk, regularly use a sunscreen with a broad spectrum SPF of 15 or higher and other sun protection measure including: Sun Protection Measures:

- apply liberally 15 minutes before sun exposure
- use a water resistant sunscreen if swimming or sweating
- reapply at least every 2 hours

- limit time in the sun, especially from 10 A.M.-2 P.M.
- wear long-sleeve shirts, pants, hats and sunglasses
- children under 6 months: Ask a doctor

Other information

Protect this product from excessive heat and direct sun

Inactive ingredients

Water, Coco-caprylate/caprate, Vitis Vinifera (Grape) Seed Oil, C15-19 Alkane, Isocetyl Stearoyl Stearate, Argania Spinosa Kernel Oil, Tocopheryl Acetate, Sodium Hyaluronate Crosspolymer, Jojoba Esters, Tribehenin, Beeswax, Glyceryl Stearate, Leuconostoc/radish Root Ferment Filtrate, Glycerin, Lactobacillus, Acacia Senegal Gum, Xanthan Gum, Viola Tricolor Extract, Bisabolol, Glycyrrhiza Glabra (Licorice) Root Extract, Sodium Hyaluronate, Aloe Barbadensis Leaf Extract, Cocos Nucifera (Coconut) Fruit Extract. Titanium Dioxide, Iron Oxides, Mica. May Contain:

Questions?

Call 877-SAIE-HEY Monday-Friday from 10 A.M.-6 P.M. EST